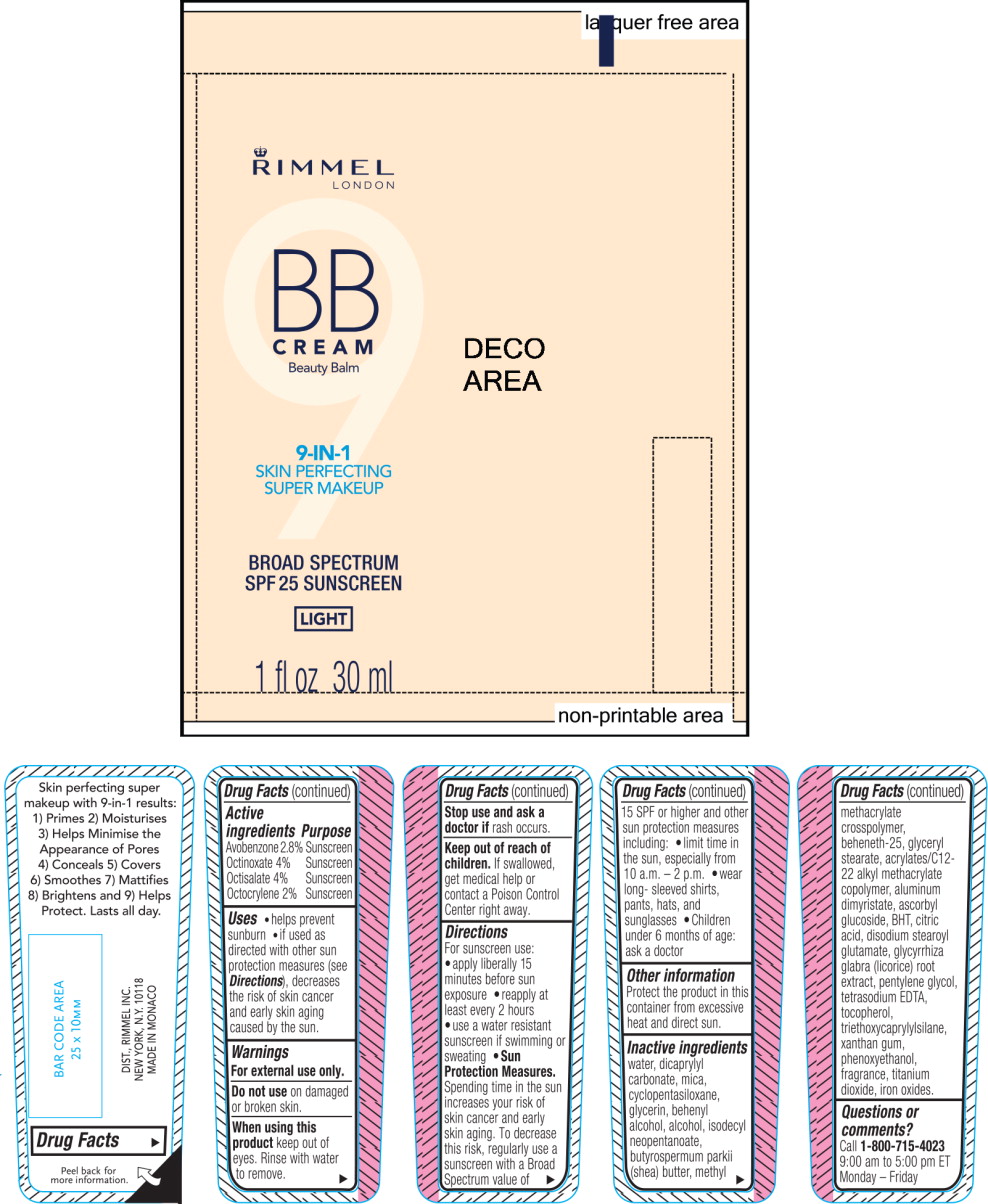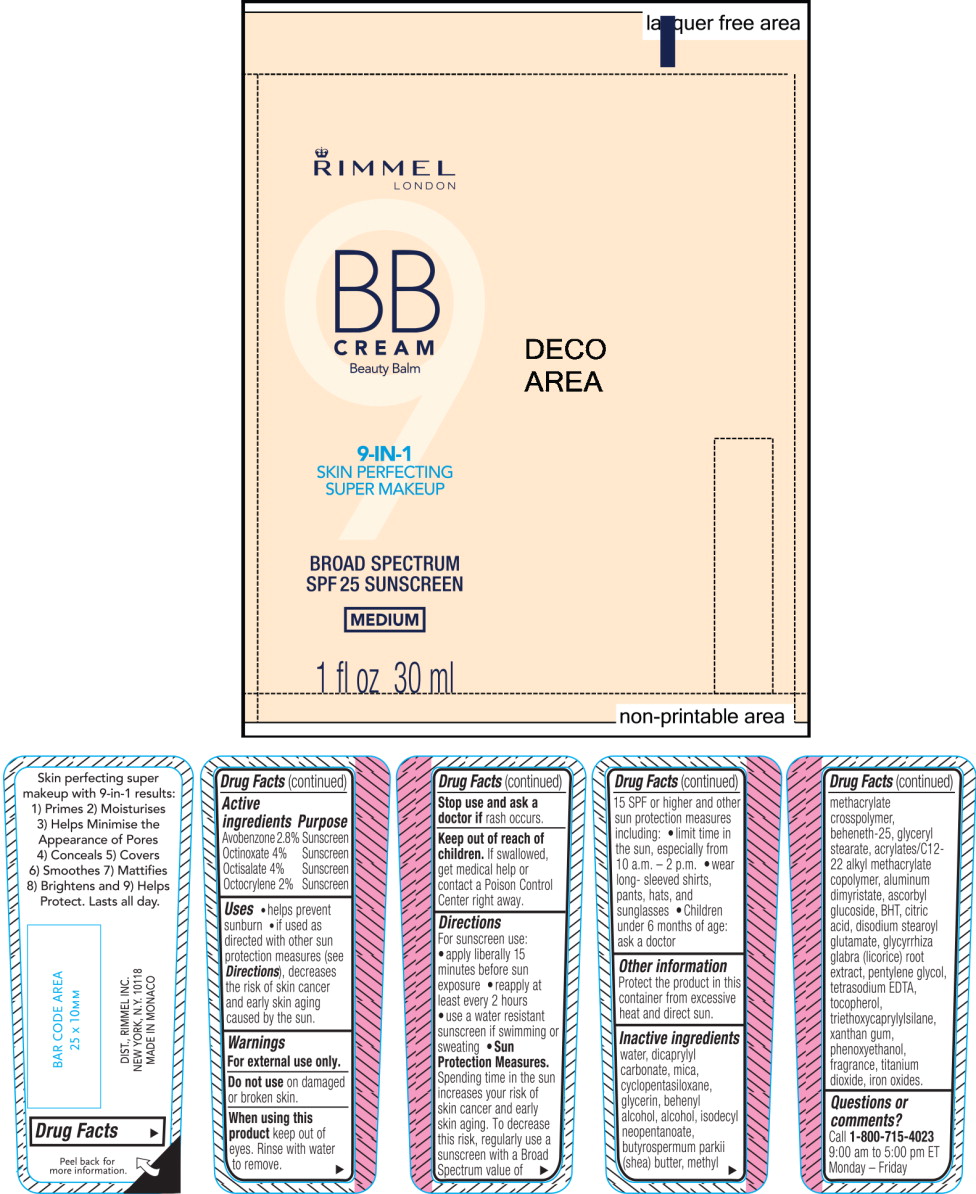 DRUG LABEL: Rimmel BB Cream 9-in-1 Skin Perfecting Super Makeup 
NDC: 76485-1070 | Form: CREAM
Manufacturer: Rimmel Inc.
Category: otc | Type: HUMAN OTC DRUG LABEL
Date: 20160907

ACTIVE INGREDIENTS: AVOBENZONE 0.9 g/30 mL; OCTINOXATE 1.3 g/30 mL; OCTISALATE 1.3 g/30 mL; OCTOCRYLENE 0.6 g/30 mL
INACTIVE INGREDIENTS: WATER; DICAPRYLYL CARBONATE; MICA; CYCLOMETHICONE 5; GLYCERIN; DOCOSANOL; ALCOHOL; ISODECYL NEOPENTANOATE; SHEA BUTTER; METHYL METHACRYLATE; BEHENETH-25; GLYCERYL MONOSTEARATE; ALUMINUM DIMYRISTATE; ASCORBYL GLUCOSIDE; BUTYLATED HYDROXYTOLUENE; CITRIC ACID MONOHYDRATE; DISODIUM STEAROYL GLUTAMATE; LICORICE; PENTYLENE GLYCOL; EDETATE SODIUM; TOCOPHEROL; TRIETHOXYCAPRYLYLSILANE; XANTHAN GUM; PHENOXYETHANOL; TITANIUM DIOXIDE; FERRIC OXIDE RED

Drug Facts

Active ingredients

Avobenzone 2.8%

Octinoxate 4%

Octisalate 4%

Octocrylene 2%

Purpose

Sunscreen

Sunscreen

Sunscreen

Sunscreen

Uses

- helps prevent sunburn
- if used as directed with other sun protection measures (see Directions), decreases the risk of skin cancer and early skin aging caused by the sun.

Warnings

For external use only

Do not use on damaged or broken skin.

When using this product keep out of eyes, Rinse with water to remove.

Stop use and ask a doctor if rash occurs.

Keep out of reach of children. If swallowed, get medical help or contact a Poison Control Center right away.

Directions

For sunscreen use:

- apply liberally 15 minutes before sun exposure
- reapply at least every 2 hours
- use a water resistant sunscreen if swimming or sweating
- Sun Protection Measures. Spending time in the sun increases your risk of skin cancer and early skin aging. To decrease this risk, regularly use a sunscreen with a Broad Spectrum value of 15 SPF or high and other sun protection measures including:
- limit time in the sun, especially from 10 a.m. - 2 p.m.
- wear long - sleeved shirts, pants, hats, and sunglasses
- Children under 6 months of age: ask a doctor

Other information

Protect the product in this container from excessive heat and direct sun.

Inactive ingredients

water, dicaprylyl carbonate, mica, cyclopentasiloxane, glycerin, behenyl alcohol, alcohol, isodecyl neopentanoate, butyrospermum parkii (shea) butter, methyl methacrylate crosspolymer, behenth-25, glyceryl stearate, acrylates/C12-22 alkyl methacrylate copolymer, aluminum dimyristate, ascorbyl glucoside, BHT, citric acid, disodium stearoyl glutamate, glycyrrhiza glabra (licorice) root extract, pentylene glycol, tetrasodium EDTA, tocopherol, triethoxycaprylylsilane, xanthan gum, phenoxyethanol, fragrance, titanium dioxide, iron oxides.

Questions or comments?

Call 1-800-715-4023

9:00 am to 5:00 pm ET

Monday - Friday

Principal Display Panel - 30 mL Bottle Light Label

RIMMEL
LONDON

BB

CREAM
Beauty Balm

9-IN-1

SKIN PERFECTING
SUPER MAKEUP

BROAD SPECTRUM

SPF25 SUNSCREEN

LIGHT

1 fl oz 30 ml

Principal Display Panel - 30 mL Bottle Medium Label

RIMMEL
LONDON

BB

CREAM
Beauty Balm

9-IN-1

SKIN PERFECTING
SUPER MAKEUP

BROAD SPECTRUM

SPF25 SUNSCREEN

MEDIUM

1 fl oz 30 ml